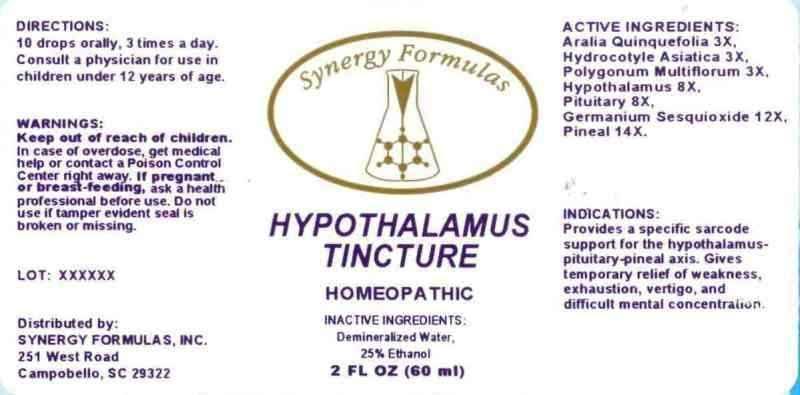 DRUG LABEL: Hypothalamus Tincture
NDC: 43772-0013 | Form: LIQUID
Manufacturer: Synergy Formulas, Inc.
Category: homeopathic | Type: HUMAN OTC DRUG LABEL
Date: 20130418

ACTIVE INGREDIENTS: AMERICAN GINSENG 3 [hp_X]/1 mL; CENTELLA ASIATICA 3 [hp_X]/1 mL; FALLOPIA MULTIFLORA ROOT 3 [hp_X]/1 mL; SUS SCROFA HYPOTHALAMUS 8 [hp_X]/1 mL; SUS SCROFA PITUITARY GLAND 8 [hp_X]/1 mL; GERMANIUM SESQUIOXIDE 12 [hp_X]/1 mL; SUS SCROFA PINEAL GLAND 14 [hp_X]/1 mL
INACTIVE INGREDIENTS: WATER; ALCOHOL

Drug Facts

ACTIVE INGREDIENTS

Aralia Quinquefolia 3X, Hydrocotyle Asiatica 3X, Polygonum Multiflorum 3X, Hypothalamus (Suis) 8X, Pituitary (Suis) 8X, Germanium Sesquioxide 12X, Pineal (Suis) 14X

INDICATIONS

Provides a specific sarcode support for the hypothalamus-pituitary-pineal axis. Gives temporary relief of weakness, exhaustion, vertigo, and difficult mental concentration.

WARNINGS

Keep out of reach of children. In case of overdose, get medical help or contact a Poison Control Center right away. If pregnant or breast-feeding, ask a health professional before use. Do not use if tamper evident seal is broken or missing.

DIRECTIONS

10 drops orally, 3 times a day. Consult a physician for use in children under 12 years of age.

INACTIVE INGREDIENTS

Demineralized Water, 25% Ethanol

KEEP OUT OF REACH OF CHILDREN

In case of overdose, get medical help or contact a Poison Control Center right away.

INDICATIONS AND USAGE

Provides a specific sarcode support for the hypothalamus-pituitary-pineal axis. Gives temporary relief of weakness, exhaustion, vertigo, and difficult mental concentration.

QUESTIONS

Distributed by:

SYNERGY FORMULAS, INC.

251 West Road

Campobello, SC 29322

PACKAGE LABEL

Synergy Formulas

HYPOTHALAMUS

TINCTURE

HOMEOPATHIC

2 FL OZ (60 ml)